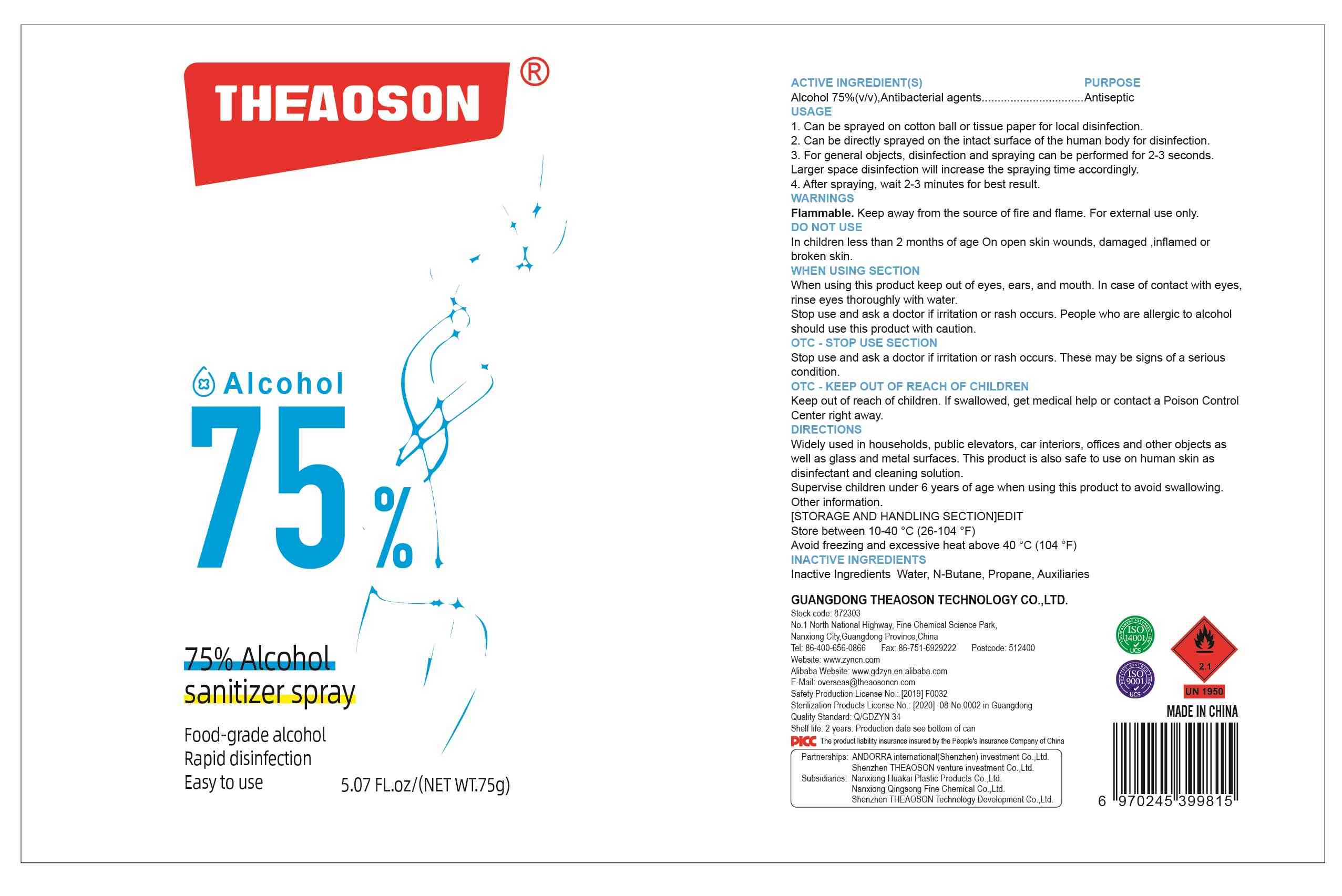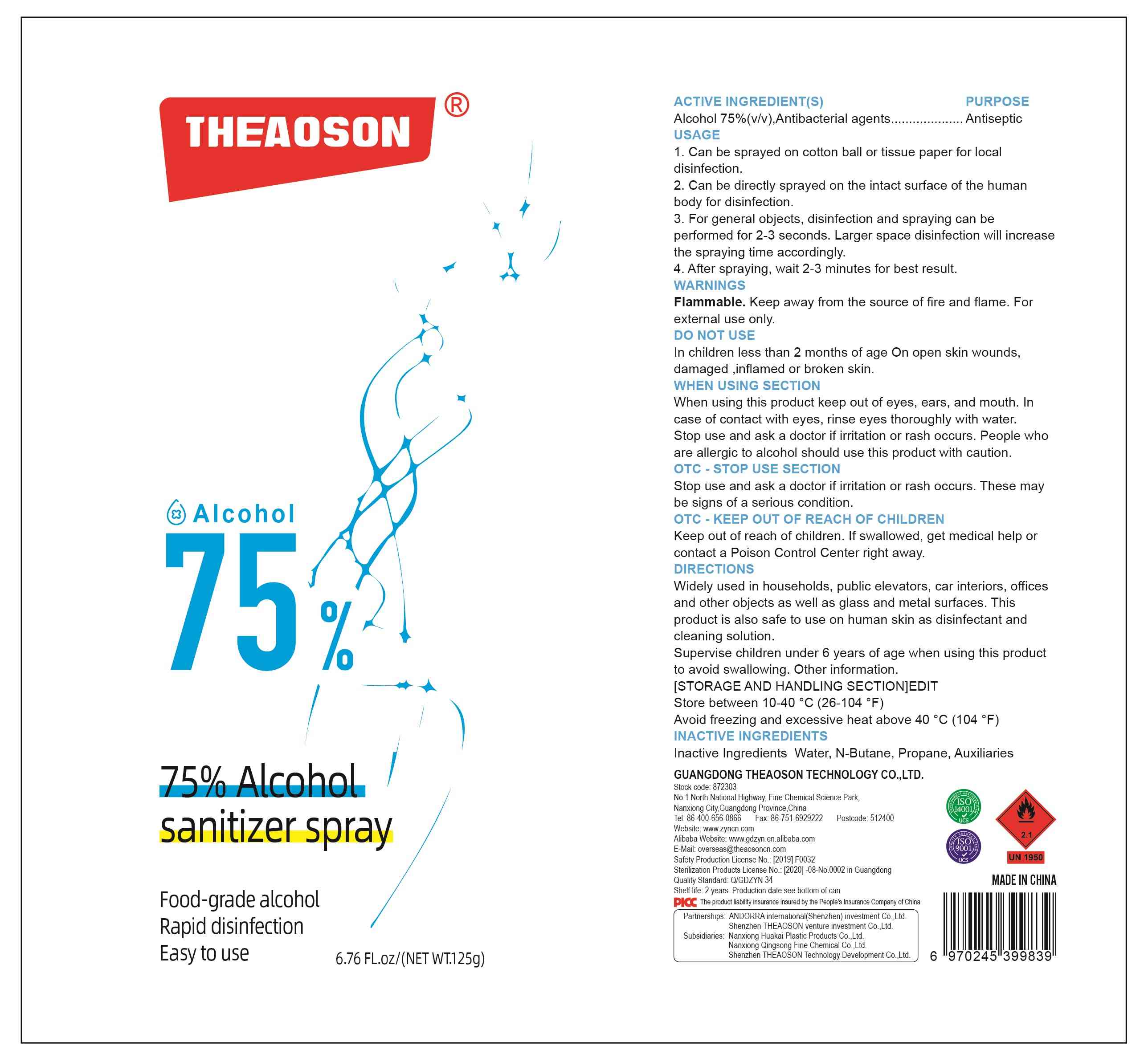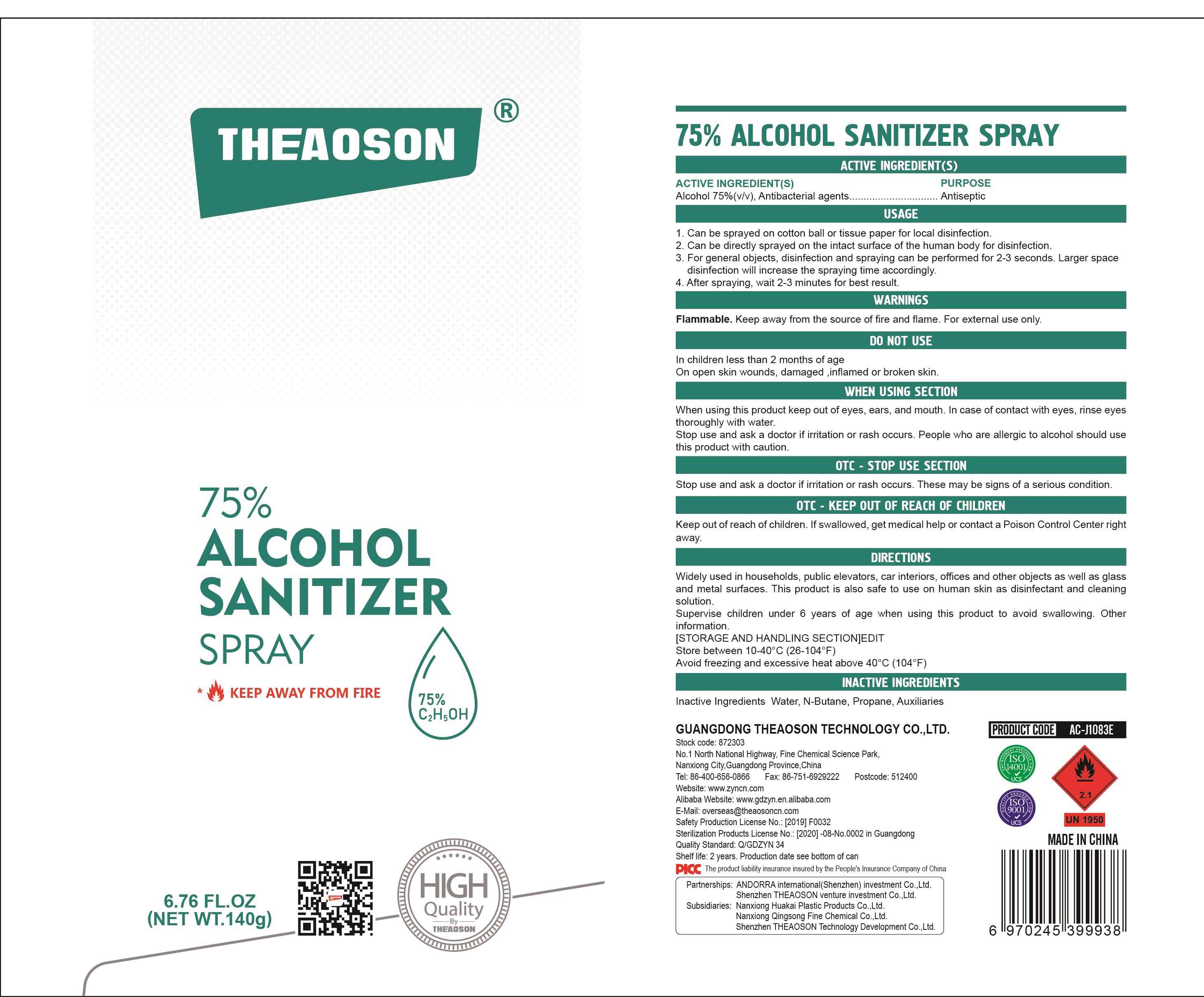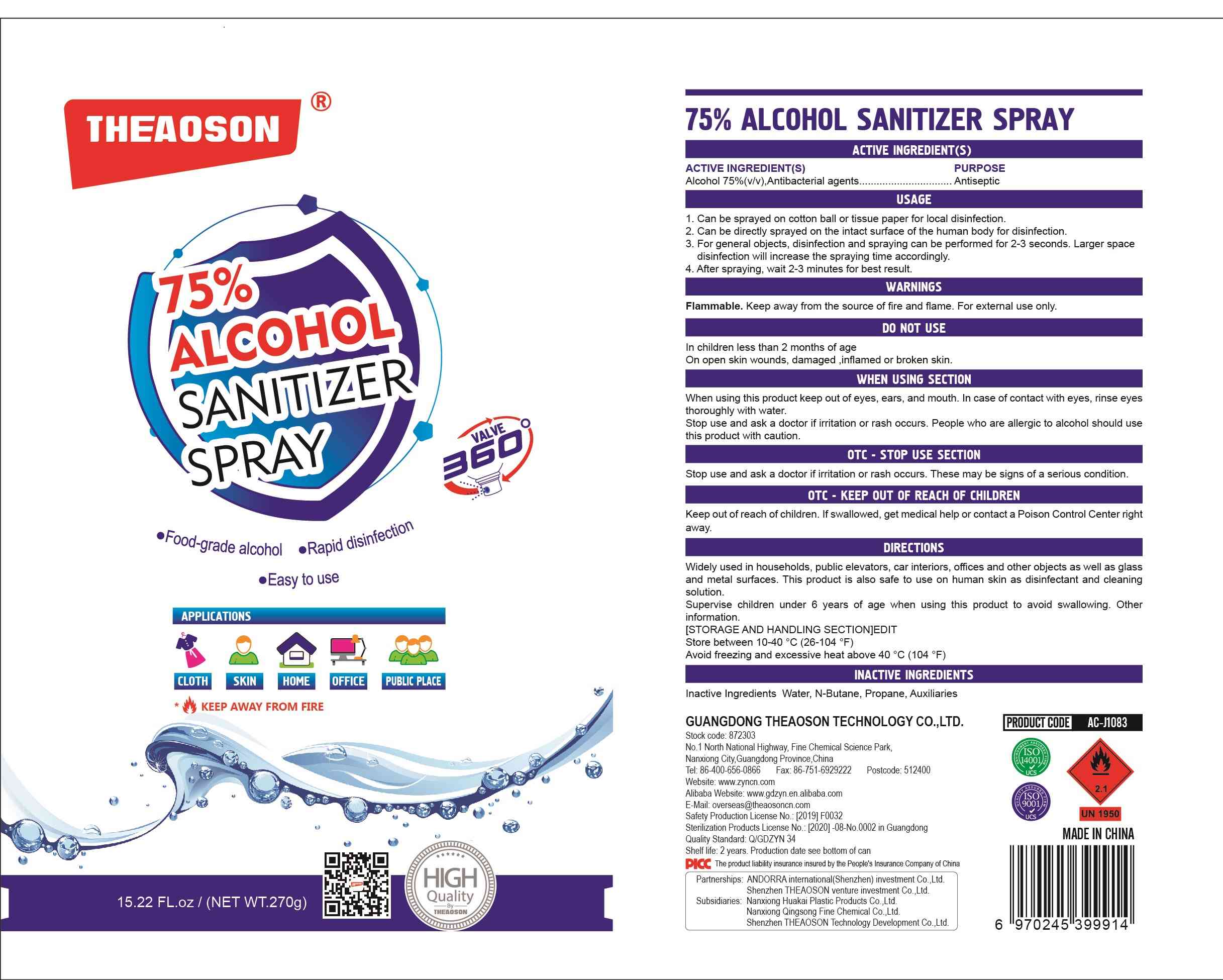 DRUG LABEL: 75% ALCOHOL SANITIZER
NDC: 78792-011 | Form: SPRAY
Manufacturer: GUANGDONG THEAOSON TECHNOLOGY CO.,LTD
Category: otc | Type: HUMAN OTC DRUG LABEL
Date: 20201215

ACTIVE INGREDIENTS: ALCOHOL 75 g/100 g
INACTIVE INGREDIENTS: BUTANE; WATER; PROPANE

78792-011
75% ALCOHOL SANITIZER SPRAY

Active Ingredient(s)

Alcohol 75%(v/v), Antibacterial agents

Purpose

Antiseptic, Hand Sanitizer

Use

1.Can be sprayed on cotton ball or tissue paper for local disinfection.
2.Can be directly sprayed on the intact surface of the human body for disinfection.
3.For general objects, disinfection and spraying can be performed for 2-3 seconds.
Larger space disinfection will increase the spraying time accordingly.
4.After spraying, wait 2-3 minutes for best result.

Warnings

Flammable.Keep away from the source of fire and flame.For external use only.

Do not use

In children less than 2 months of age On open skin wounds, damaged, inflamed or broken skin.

When using this product keep out of eyes, ears, and mouth.In case of contact with eyes, rinse eyes thoroughly with water.
Stop use and ask a doctor if irritation or rash occurs.People who are allergic to alcohol should use this product with caution.

Stop use and ask a doctor if irritation or rash occurs.These maybe signs of a serious condition.

Keep out of reach of children.If swallowed, get medical help or contact a Poison Control Center right away.

Directions

Widely used in households, public elevators, car interiors, offices and other objects as well as glass and metal surfaces.This product is also safe to use on human skin as disinfectant and cleaning solution.
Supervise children under 6 years of age when using this product to avoid swallowing.

Other information

[STORAGE AND HANDLING SECTION] EDIT
Store between 10-40°C(26-104°F)
Avoid freezing and excessive heat above 40°C(104°F)

Inactive ingredients

Water, N-Butane, Propane, Auxiliaries

Package Label - Principal Display Panel

78792-011-01 75g

78792-011-02 125g

78792-011-03 140g

78792-011-04 270g